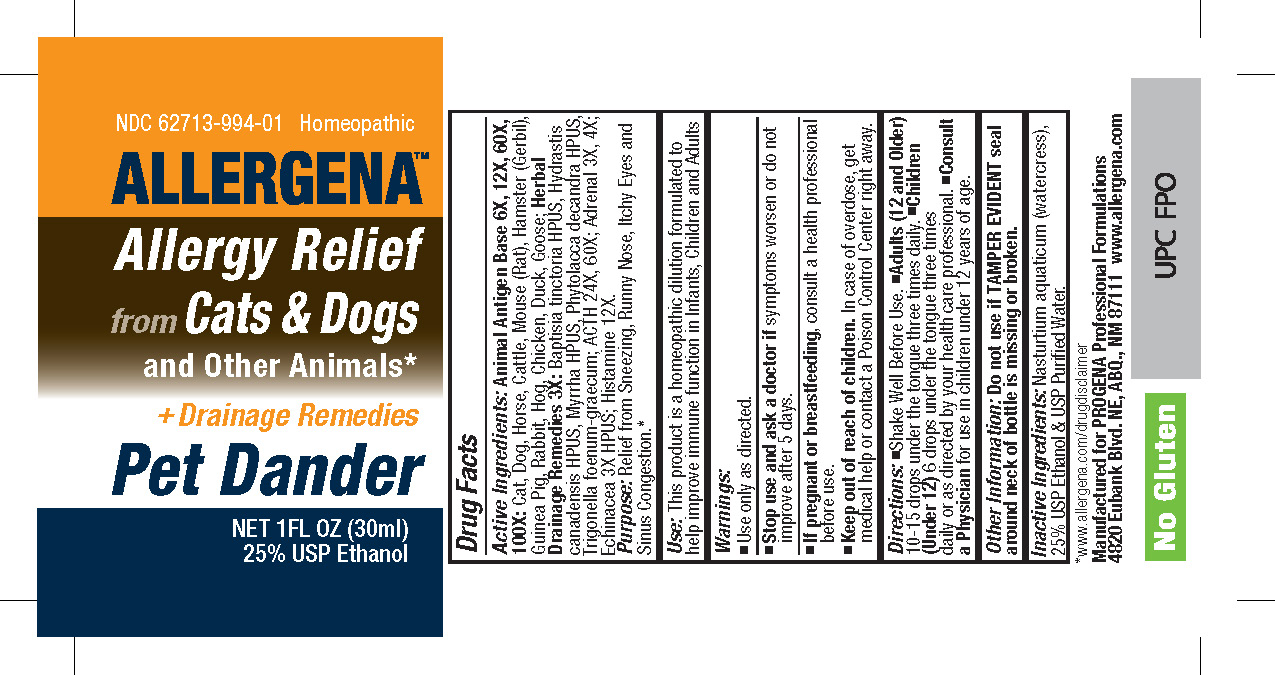 DRUG LABEL: Allergena Pet Dander

NDC: 62713-994 | Form: LIQUID
Manufacturer: Meditrend, Inc. DBA Progena Professional Formulations
Category: homeopathic | Type: HUMAN OTC DRUG LABEL
Date: 20250128

ACTIVE INGREDIENTS: BOS TAURUS ADRENAL GLAND 4 [hp_X]/1 mL; ECHINACEA ANGUSTIFOLIA 3 [hp_X]/1 mL; MAMMAL LIVER 12 [hp_X]/1 mL; CORTICOTROPIN 30 [hp_X]/1 mL; HISTAMINE 12 [hp_X]/1 mL; FELIS CATUS DANDER 100 [hp_X]/1 mL; CANIS LUPUS FAMILIARIS DANDER 100 [hp_X]/1 mL; EQUUS CABALLUS DANDER 100 [hp_X]/1 mL; BOS TAURUS DANDER 100 [hp_X]/1 mL; MUS MUSCULUS SKIN 100 [hp_X]/1 mL; MESOCRICETUS AURATUS SKIN 100 [hp_X]/1 mL; CAVIA PORCELLUS DANDER 100 [hp_X]/1 mL; ORYCTOLAGUS CUNICULUS SKIN 100 [hp_X]/1 mL; SUS SCROFA DANDER 100 [hp_X]/1 mL; CHICKEN 100 [hp_X]/1 mL; DUCK 100 [hp_X]/1 mL; GOOSE 100 [hp_X]/1 mL; BAPTISIA TINCTORIA 3 [hp_X]/1 mL; GOLDENSEAL 3 [hp_X]/1 mL; MYRRH 3 [hp_X]/1 mL; PHYTOLACCA AMERICANA ROOT 3 [hp_X]/1 mL; FENUGREEK SEED 3 [hp_X]/1 mL
INACTIVE INGREDIENTS: ALCOHOL; WATER; NASTURTIUM OFFICINALE

Allergena Pet Dander

ACTIVE INGREDIENT

Active Ingredients: Animal Antigen Base 6X, 12X, 60X, 100X:Cat, Dog, Horse, Cattle, Mouse (Rat), Hamster (Gerbil), Guinea Pig, Rabbit, Hog, Chicken, Duck, Goose; Herbal Drainage Remedies 3X:Baptisia tinctoria HPUS; Hydrastis canadensis HPUS; Myrrha HPUS; Phytolacca decandra HPUS; Trigonella foenum-graecum. ACTH 24x, 60x; Adrenal 3X, 4X; Echinacea 3X HPUS; Histamine 12X.

PURPOSE

Purpose: Relief from Sneezing, Runny Nose, Itchy Eyes and Sinus Congestion.*

Keep Out of Reach of Children.In case of overdose, get medical help or contact a
Poison Control Center right away.

INDICATIONS AND USAGE

Use: This product is a Homeopathic Dilution formulated to help improve immune function in Infants, Children and Adults.*

Warnings:

- Use Only as directed.
- Stop use and ask a doctor if symptoms worsen or do not improve after 5 days.
- If pregnant or breast-feeding, consult a health professional before use.

DOSAGE AND ADMINISTRATION

Directions: • Shake Well Before Use. • Adults (12 and Older) 10-15 drops under the tongue three times daily. • Children (Under 12) 6 drops under the tongue three times daily or as directed by your health care professional. • Consult a Physicianfor use in children under 12 years of age.

Other Information: Do not use if TAMPER EVIDENT seal around neck of bottle is missing or broken.

INACTIVE INGREDIENT

Inactive Ingredients: Nasturtium aquaticum (watercress), 25% USP Ethanol & USP Purified Water.

PACKAGE LABEL

*www.allergena.com/drugdisclaimer

Manufactured for Progena Professional Formulations
4820 Eubank Blvd. NE, ABQ, NM 87111, www.allergena.com